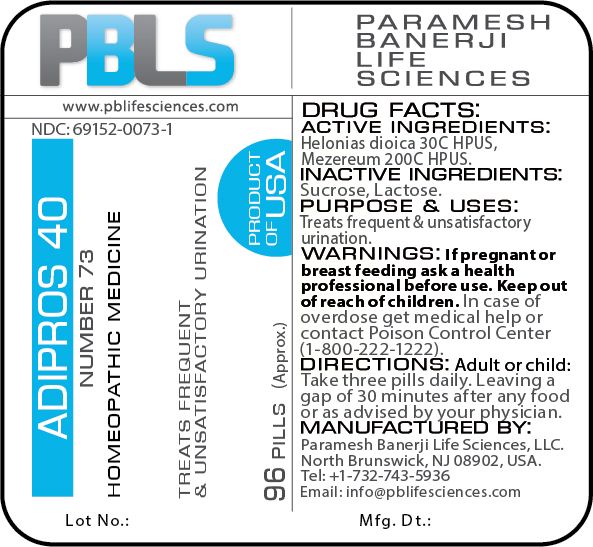 DRUG LABEL: Adipros 40 (number 73)
NDC: 69152-0073 | Form: PELLET
Manufacturer: Paramesh Banerji Life Sciences LLC
Category: homeopathic | Type: HUMAN OTC DRUG LABEL
Date: 20180626

ACTIVE INGREDIENTS: CHAMAELIRIUM LUTEUM ROOT 30 [hp_C]/1 1; DAPHNE MEZEREUM BARK 200 [hp_C]/1 1
INACTIVE INGREDIENTS: SUCROSE; LACTOSE

DRUG FACTS: Active Ingredients

Helonias dioica 30C HPUS, Mezereum 200C HPUS

Inactive Ingredients

Sucrose, Lactose

Purpose

Treats frequent & unsatisfactory urination

Uses

Treats frequent & unsatisfactory urination

Warnings

If pregnant or breast feeding ask a health professional before use.

Keep out of reach of children. In case of overdose, get medical help or contact a Poison Control Center (1-800-222-1222) right away.

Direction

Adult or child: Take three pills daily. Leaving a gap of 30 minutes after any food or as advised by your physician.

Manufactured by

Paramesh Banerji Life Sciences, LLC.

North Brunswick, NJ 08902, USA.

Tel: +1-732-743-5936

Email: info@pblifesciences.com

Principal Display Panel

NDC: 69152-0073-1

Adipros 40

Number 73

Homeopathic Medicine

Treats frequent and unsatisfactory urination

96 Pills (Approx.)

Product of USA